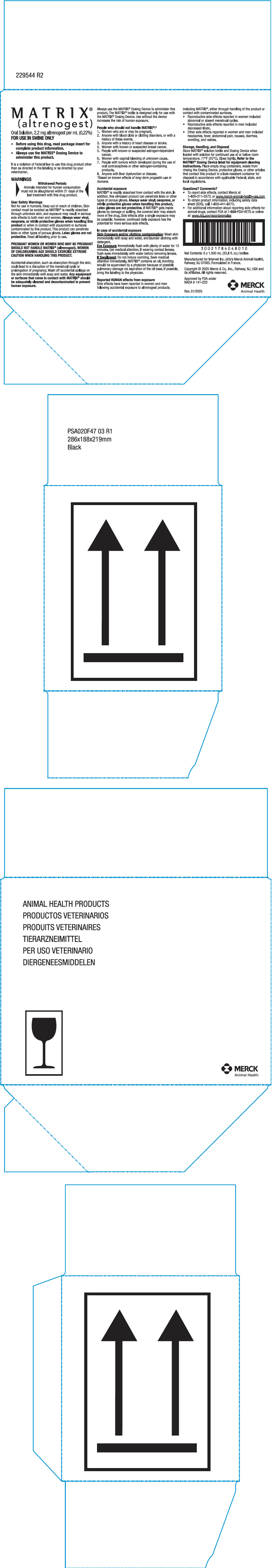 DRUG LABEL: Matrix
NDC: 57926-101 | Form: SOLUTION
Manufacturer: Merck Sharp & Dohme Corp.
Category: animal | Type: OTC ANIMAL DRUG LABEL
Date: 20250429

ACTIVE INGREDIENTS: ALTRENOGEST 2.2 mg/1 mL

MATRIX® (altrenogest)

VETERINARY INDICATIONS

Oral solution, 2.2 mg altrenogest per mL (0.22%) Synthetic progestin

For Use in Swine Only

USES:

For synchronization of estrus in sexually mature gilts that have had at least one estrous cycle. Treatment with MATRIX® results in estrus (standing heat) 4 to 9 days after completion of the 14-day treatment period.

It is a violation of Federal law to use this drug product other than as directed in the labeling or as directed by your veterinarian.

DESCRIPTION:

MATRIX® (altrenogest) Oral Solution contains 2.2 mg altrenogest per mL (0.22%) in an oil solution.

WARNINGS

WARNINGS:

WITHDRAWAL PERIODS
Animals intended for human consumption must not be slaughtered within 21 days of the last treatment with this drug product.

USER SAFETY WARNINGS:

Not for use in humans. Keep out of reach of children.

Skin contact must be avoided as MATRIX® is readily absorbed through unbroken skin, and exposure may result in serious side effects to both women and men. Always wear vinyl, neoprene, or nitrile protective gloves when handling MATRIX or when in contact with equipment or surfaces contaminated by this product. Latex gloves are not protective.

PREGNANT WOMEN OR WOMEN WHO MAY BE PREGNANT SHOULD NOT HANDLE MATRIX® (altrenogest). WOMEN OF CHILDBEARING AGE SHOULD EXERCISE EXTREME CAUTION WHEN HANDLING THIS PRODUCT.

Accidental absorption, such as absorption through the skin, could lead to a disruption of the menstrual cycle or prolongation of pregnancy. Wash off accidental spillage on the skin immediately with soap and water. Any equipment or surfaces that come in contact with MATRIX® should be adequately cleaned and decontaminated to prevent human exposure.

Always use the MATRIX® Dosing Device to administer this product. The MATRIX® bottle is designed only for use with the MATRIX® Dosing Device. Use without the device increases the risk of human exposure.

PEOPLE WHO SHOULD NOT HANDLE MATRIX®: [Based on known effects of long-term progestin use in humans.]

1. Women who are or may be pregnant.
2. Anyone with blood clots or clotting disorders, or with a history of these events.
3. Anyone with a history of heart disease or stroke.
4. Women with known or suspected breast cancer.
5. People with known or suspected estrogen-dependent cancer.
6. Women with vaginal bleeding of unknown cause.
7. People with tumors which developed during the use of oral contraceptives or other estrogen-containing products.
8. Anyone with liver dysfunction or disease.

ACCIDENTAL EXPOSURE:

MATRIX® is readily absorbed from contact with the skin. In addition, this oil-based product can penetrate latex or other types of porous gloves. Always wear vinyl, neoprene, or nitrile protective gloves when handling MATRIX®. Latex gloves are not protective. If MATRIX® gets inside gloves by damage or spilling, the covered skin may absorb more of the drug. Side effects after a single exposure are possible; however, continued daily exposure has the potential for more serious effects.

IN CASE OF ACCIDENTAL EXPOSURE:

Skin exposure and/or clothing contamination: Wash skin immediately with soap and water, and launder clothing with detergent.

Eye exposure: Immediately flush with plenty of water for 15 minutes. Get medical attention. If wearing contact lenses, flush eyes immediately with water before removing lenses.

If swallowed: Do not induce vomiting. Seek medical attention immediately. MATRIX® contains an oil. Vomiting should be supervised by a physician because of possible pulmonary damage via aspiration of the oil base. If possible, bring the labeling to the physician.

Reported HUMAN Effects from Exposure:

Side effects have been reported in women and men following accidental exposure to altrenogest products, including MATRIX®, either through handling of the product or contact with contaminated surfaces.

- Reproductive side effects reported in women included abnormal or absent menstrual cycles.
- Reproductive side effects in men included decreased libido.
- Other side effects reported in women and men included headaches, fever, abdominal pain, nausea, diarrhea, vomiting, and rashes.

ANIMAL SAFETY WARNINGS:

Do not use MATRIX® in gilts having a previous or current history of uterine inflammation (i.e., acute, subacute, or chronic endometritis).

Underdosing of MATRIX® may lead to the occurrence of cystic follicles.

OTHER EFFECTS YOU MAY NOTICE:

A small percentage (less than 5%) of treated gilts may exhibit estrus (standing heat) during the 14-day treatment period. Gilts nearing estrus at the start of the 14-day treatment period may express estrus early in that period.

DIRECTIONS:

While wearing vinyl, neoprene, or nitrile gloves, remove shipping cap and seal; replace with enclosed plastic dispensing cap. This product can penetrate latex or other types of porous gloves. Latex gloves are not protective. Connect the MATRIX® Dosing Device to the solution bottle, according to the instructions provided with the MATRIX® Dosing Device package. Do not use any dosing device other than the MATRIX® Dosing Device.

Administer 6.8 mL (15 mg altrenogest) per gilt once daily for 14 consecutive days. Treat gilts on an individual animal basis by top-dressing MATRIX® on a portion of each gilt's daily feed allowance. To produce the desired synchronization of estrus in a group of gilts, treat all of the gilts daily for the same 14-day period.

HOW SUPPLIED:

MATRIX® (altrenogest) Oral Solution contains 2.2 mg/mL (0.22%) of the active ingredient, packaged in 1,000 mL plastic bottles.

STORAGE, HANDLING, AND DISPOSAL:

Store MATRIX® solution bottle and Dosing Device when loaded with solution for continued use at or below room temperature, 77°F (25°C). Close tightly. Refer to the MATRIX® Dosing Device label for equipment cleaning instructions. Place empty drug containers, waste from rinsing the Dosing Device, protective gloves, or other articles that contact this product in a leak-resistant container for disposal in accordance with applicable Federal, state, and local regulations.

QUESTIONS? COMMENTS?

- To report side effects, contact Merck at 1-800-211-3573, or online at www.merck-animal-health-usa.com
- To obtain product information, including a safety data sheet (SDS), call 1-800-441-8272.
- For additional information about reporting side effects for animal drugs, contact FDA at 1-888-FDA-VETS or online at: www.fda.gov/reportanimalae

Approved by FDA under NADA # 141-222

Restricted Drug (California) - use only as directed.

Manufactured for Intervet Inc. (d/b/a Merck Animal Health), Rahway, NJ 07065, a subsidiary of Merck & Co.

Copyright © 2025 Merck & Co., Inc., Rahway, NJ, USA and its affiliates.
All rights reserved.

Altrenogest (active ingred.) made in: see imprint.

Formulated in France.
Rev. 01/2025

PRINCIPAL DISPLAY PANEL - 1000 mL Bottle Carton

MATRIX®
(altrenogest)

Oral Solution, 2.2 mg altrenogest per mL (0.22%)
FOR USE IN SWINE ONLY

- Before using this drug, read package insert for
  complete product information.
- Always use the MATRIX® Dosing Device to
  administer this product.

It is a violation of Federal law to use this drug product other
than as directed in the labeling or as directed by your
veterinarian.